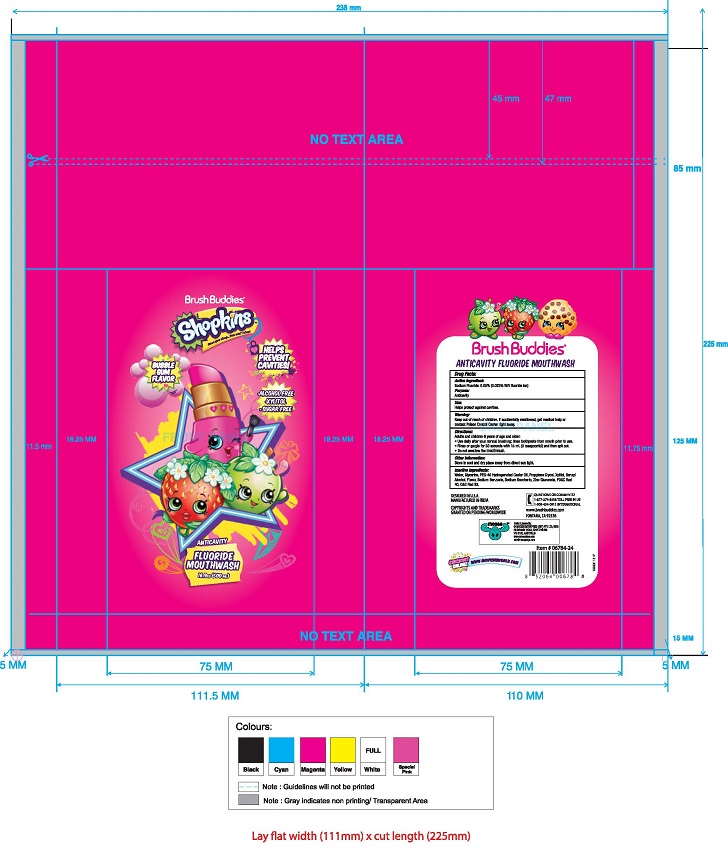 DRUG LABEL: Shopkins Mouth wash
NDC: 70108-008 | Form: LIQUID
Manufacturer: Ashtel Studios Inc.
Category: otc | Type: HUMAN OTC DRUG LABEL
Date: 20191231

ACTIVE INGREDIENTS: SODIUM FLUORIDE 0.05 mg/100 g
INACTIVE INGREDIENTS: HYDROGENATED CASTOR OIL; CITRAL PROPYLENE GLYCOL ACETAL; ZINC GLUCONATE; SODIUM PHOSPHATE, TRIBASIC, DODECAHYDRATE; WATER; .ALPHA.-(.ALPHA.-AMINOPROPYL)BENZYL ALCOHOL HYDROCHLORIDE, ERYTHRO-(+/-)-; GLYCERIN; XYLITOL; SODIUM BENZOATE; SACCHARIN SODIUM

Shopkins Mouth wash

PURPOSE

Anticavity

Keep out of reach of children. In case of accidental digestion seek professional assistance or contact a poison control center immediately.

Active Ingredient Purpose

Sodium Fluoride 0.5% (0.23% w/v fluoride ion) ......................... Anticavity

INDICATIONS AND USAGE

Helps protect teeth and roots against cavities

keep out of reach of children.

If you accidentally swallow seek medical help or contact a poison control center immediately

INACTIVE INGREDIENT

Water, Glycerine,PEG-40 Hydrogenated Castor Oil,Propylene Glycol,Xylitol,Benzyl Alcohol, Flavor, Sodium Benzoate, Sodium Saccharin, Zinc Gluconate, FD&C Red 40, D&C Red 33

DOSAGE AND ADMINISTRATION

Adults and children 6 years and older:
Use daily after your normal brushing. Rinse toothpaste from your mouth prior to ouse.

Rinse or gargle for 30 seconds with 15ml (3 teaspoonful) and then spit it out.

Do not swallow the mouth wash